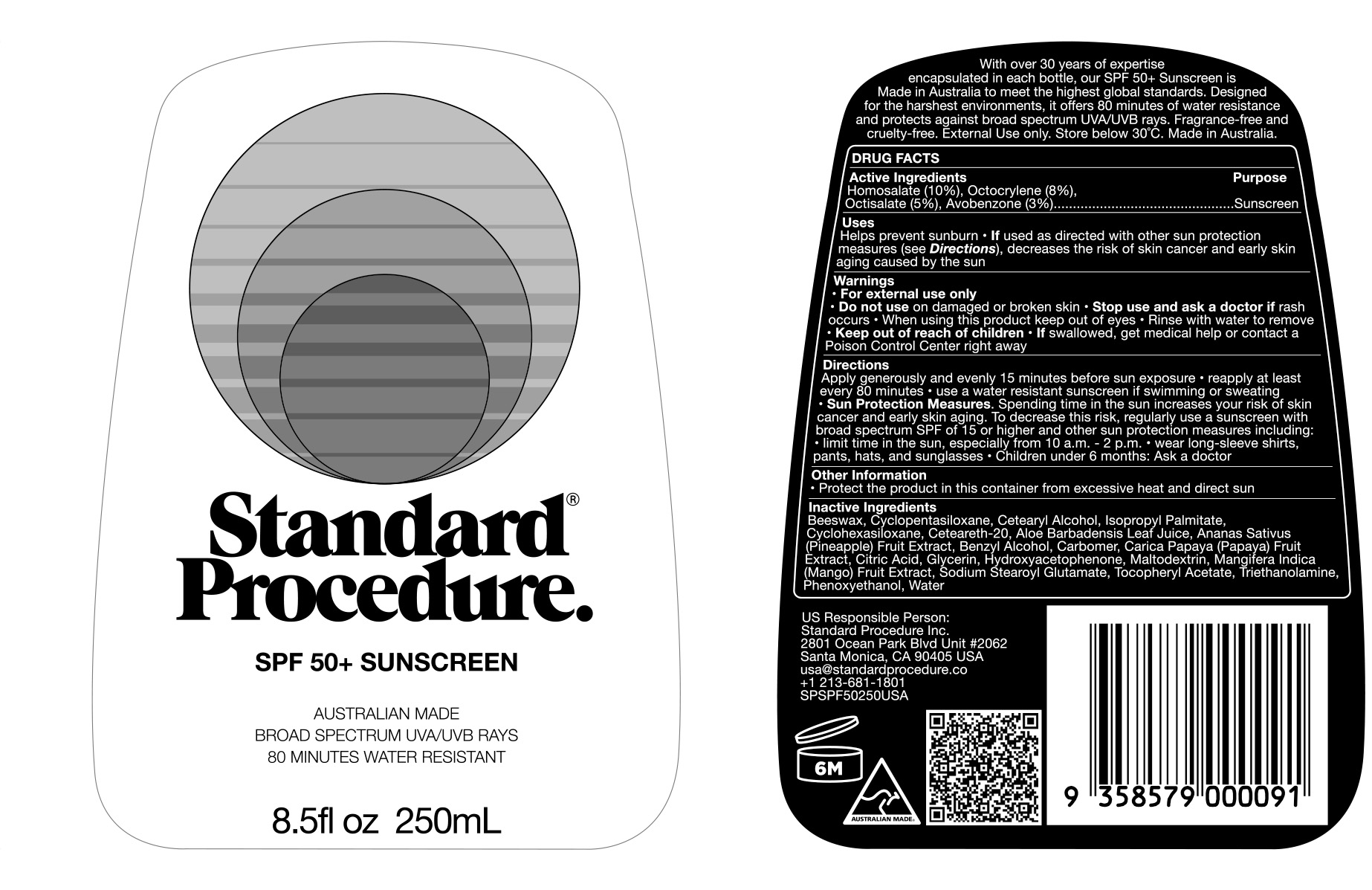 DRUG LABEL: Standard Procedure SPF 50 Sunscreen
NDC: 84425-101 | Form: LOTION
Manufacturer: Standard Procedure Inc
Category: otc | Type: HUMAN OTC DRUG LABEL
Date: 20260114

ACTIVE INGREDIENTS: OCTOCRYLENE 80 mg/1 mL; AVOBENZONE 30 mg/1 mL; HOMOSALATE 100 mg/1 mL; OCTISALATE 50 mg/1 mL
INACTIVE INGREDIENTS: MALTODEXTRIN; CARBOMER HOMOPOLYMER, UNSPECIFIED TYPE; SODIUM STEAROYL GLUTAMATE; PEG-8 BEESWAX; PHENOXYETHANOL; WATER; ISOPROPYL PALMITATE; GLYCERIN; HYDROXYACETOPHENONE; CITRIC ACID MONOHYDRATE; TROLAMINE; .ALPHA.-TOCOPHEROL ACETATE; CETOSTEARYL ALCOHOL; CYCLOMETHICONE 6; ALOE VERA LEAF; CYCLOMETHICONE 5; BENZYL ALCOHOL; MANGO; POLYOXYL 20 CETOSTEARYL ETHER; PAPAYA

Active Ingredients

Homosalate 10%

Octocrylene 8%

Octisalate 5%

Avobenzone 3%

Purpose

Sunscreen

Uses

Helps prevent sunburn

If used as directed with other sun protection measures (see Directions), decrease the risk of skin cancer and early skin aging caused by the sun.

Warnings

- For external use only
- Do not use on damaged orbroken skin
- Stop use and ask a doctor if rash occurs
- When using this product keep out of eyes
- Rinse with water to remove

Keep out of reach of children. If swallowed, get medical help or contact Poison Control Center right away.

Directions

- Apply generously and evenly 15 minutes before sun exposure
- Reapply at least every 80 minutes
- Usa a water resistant sunscreen if swimming or sweating
- Sun Protection Measures.
  Speading time in the sun increases your risk of skin cancer and early skin aging. To decres this risk, regularly usa a sunscreen with broad spectum SPF of 15 or higher and other sun protection measures including:
  Limit time in thee sun, especially from 10 a.m. - 2 p.m, wear long-sleeve shirts, pants, hats and sunglasses, children under 6 months: Ask a doctor

Other Information

Protect the product in this container from exessive heat and direct sun

Inactive Ingredients

BEESWAX, CYCLOPENTASILOXANE, CETEARYL ALCOHOL, ISOPROPYL PALMITATE, CYCLOHEXASILOXANE, CETEARETH-20, ALOE BARBADENSIS LEAF JUICE, ANANAS SATIVUS (PINEAPPLE) FRUIT EXTRACT, BENZYL ALCOHOL, CARBOMER, CARICA PAPAYA (PAPAYA) FRUIT EXTRACT, CITRIC ACID, GLYCERIN, HYDROXYACETOPHENONE, MALTODEXTRIN, MANGIFERA INDICA (MANGO) FRUIT EXTRACT, SODIUM STEAROYL GLUTAMATE, TOCOPHERYL ACETATE, TRIETHANOLAMINE, PHENOXYETHANOL, WATER

Contact

Standard Procedure Inc

2801 Ocean Park Blvd Unit #2062

Santa Monica CA 90405 USA

usa@standardprocedure.co

+1 213-681-1801

PACKAGE LABEL.PRINCIPAL DISPLAY PANEL

Standard Procedure.

SPF 50+ Sunscreen

Australian Made

Broad Spectrum UVA/UVB Rays

80 minutes Water Resistant